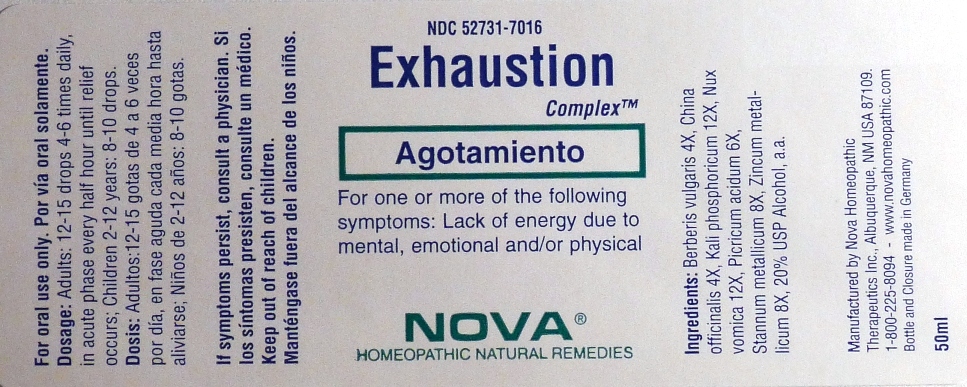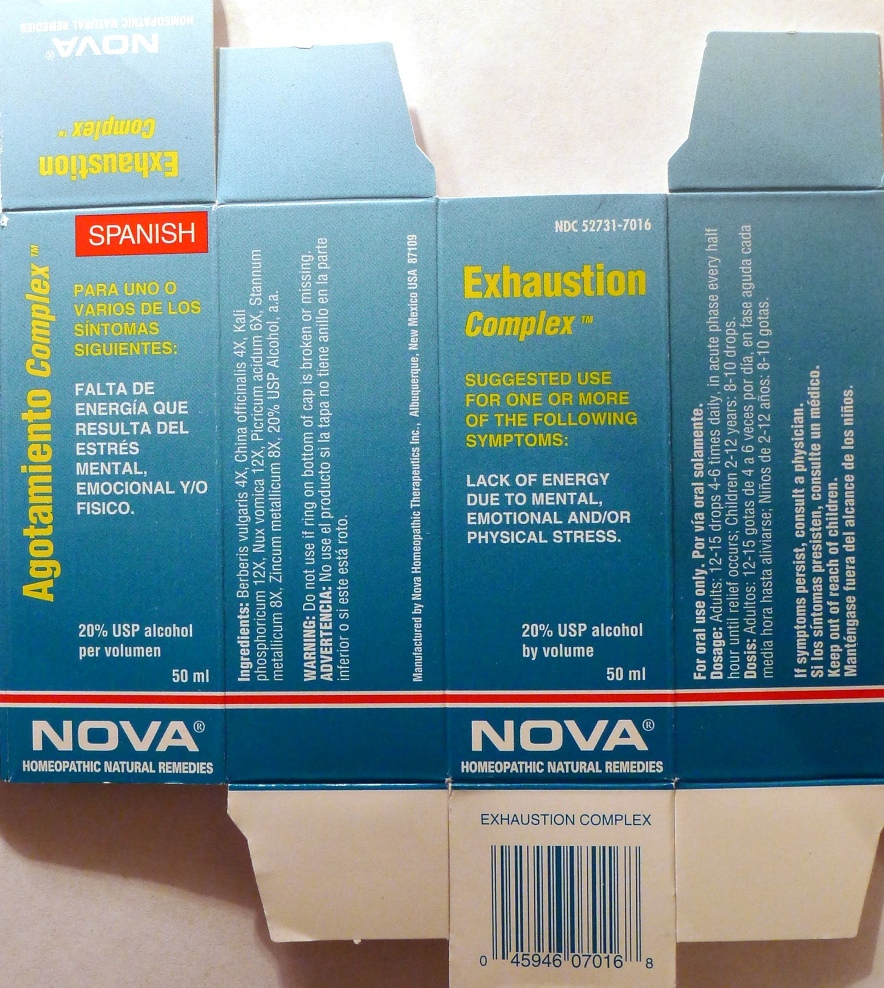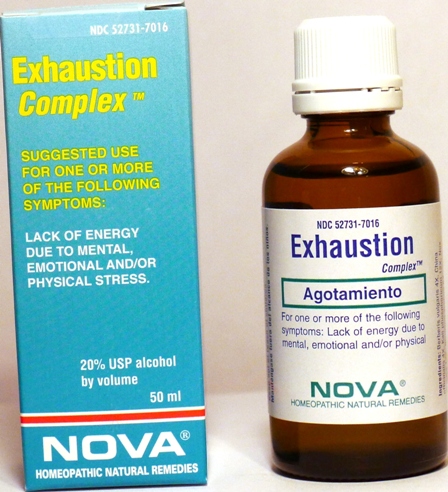 DRUG LABEL: Exhaustion Complex
NDC: 52731-7016 | Form: LIQUID
Manufacturer: Nova Homeopathic Therapeutics, Inc.
Category: homeopathic | Type: HUMAN OTC DRUG LABEL
Date: 20110601

ACTIVE INGREDIENTS: BERBERIS VULGARIS ROOT BARK 4 [hp_X]/1 mL; CINCHONA PUBESCENS BARK 4 [hp_X]/1 mL; POTASSIUM PHOSPHATE, DIBASIC 12 [hp_X]/1 mL; STRYCHNOS NUX-VOMICA SEED 12 [hp_X]/1 mL; TRINITROPHENOL 6 [hp_X]/1 mL; TIN 8 [hp_X]/1 mL; ZINC 8 [hp_X]/1 mL
INACTIVE INGREDIENTS: ALCOHOL

Exhaustion Complex

Purpose:

Suggested use for one or more of the following symptoms:

Lack of energy due to mental,emotional and/or physical stress.

Usage and Dosage:

For oral use only.

DOSAGE AND ADMINISTRATION

Adults:
In Acute Phase:
12-15 drops, every half hour until relief occurs
When Relief Occurs:
12-15 drops, 4-6 times per day
Children 2-12 years:
8-10 drops, 4-6 times per day

Warnings:

Keep out of reach of children.

WARNINGS

If symptoms persist, consult a physician.
Do not use if ring on bottom of cap is broken or missing.

Active Ingredients:

Berberis vulgaris 4X, China officinalis 4X, Kali phosphoricum 12X, Nux vomica 12X, Picricum acidum 6X, Stannum metallicum 8X, Zincum metallicum 8X

Inactive Ingredients:

Alcohol, 20% USP

QUESTIONS

Manufactured by Nova Homeopathic Therapeutics Inc., Albuquerque, New Mexico USA 87109
1-800-225-8094

PACKAGE LABEL

Exhaustion Complex Product

Exhaustion Complex Bottle Label

Exhaustion Complex Box